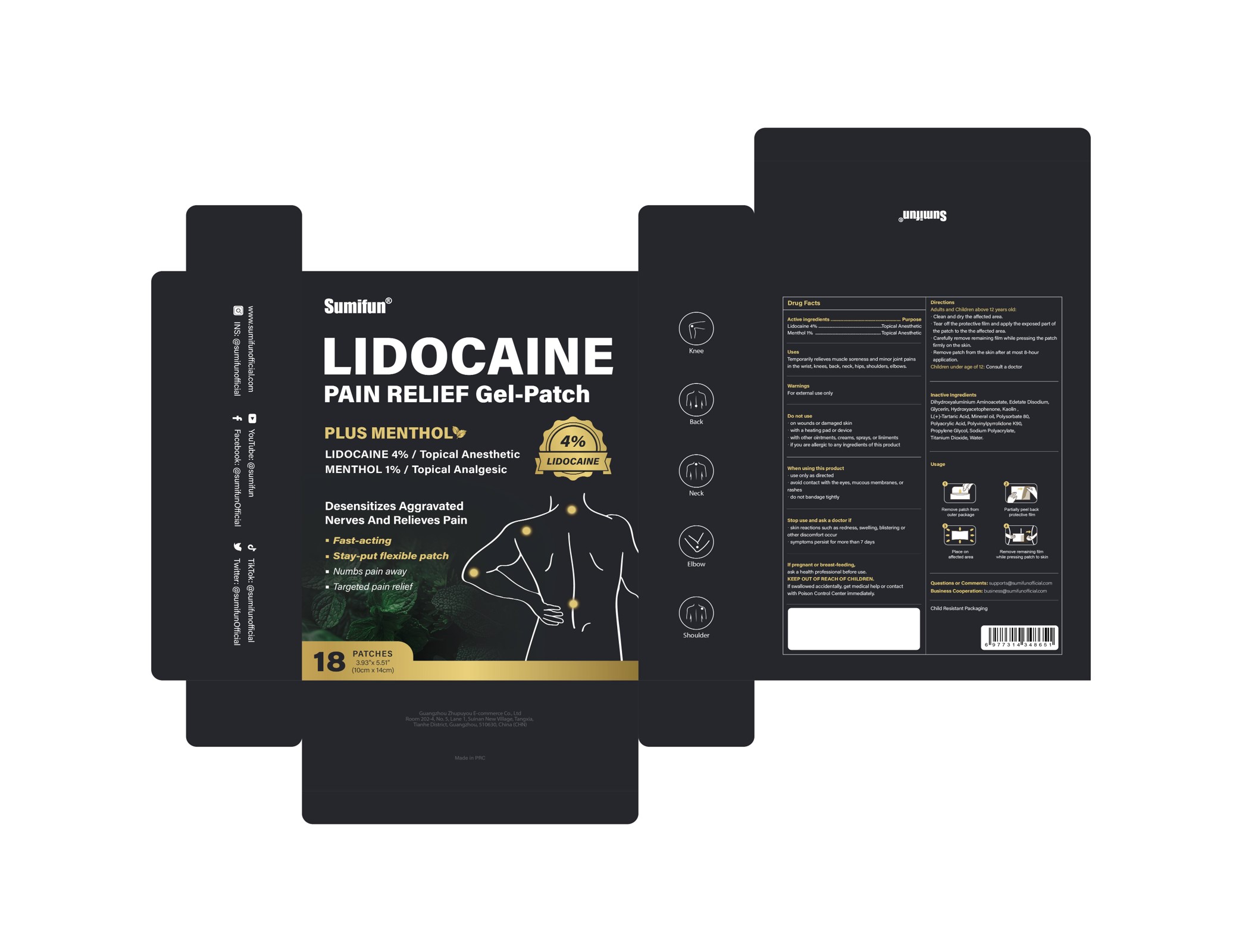 DRUG LABEL: PAIN RELIEF Gel-Patch
NDC: 84165-104 | Form: PATCH
Manufacturer: Guangzhou Zhupuyou E-commerce Co., Ltd
Category: otc | Type: HUMAN OTC DRUG LABEL
Date: 20260108

ACTIVE INGREDIENTS: MENTHOL 0.01 g/1 g; LIDOCAINE 0.04 g/1 g
INACTIVE INGREDIENTS: TITANIUM DIOXIDE; DIHYDROXYALUMINUM AMINOACETATE ANHYDROUS; EDETATE DISODIUM; PROPYLENE GLYCOL; POLYSORBATE 80; GLYCERIN; KAOLIN; POVIDONE K90; MINERAL OIL; POLYACRYLIC ACID (250000 MW); WATER; TARTARIC ACID; SODIUM POLYACRYLATE (2500000 MW); HYDROXYACETOPHENONE

84165-104 PAIN RELIEF Gel-Patch

PAIN RELIEF Gel-Patch

ACTIVE INGREDIENT

Lidocaine 4%
Menthol 1%

PURPOSE

Topical Anesthetic

INDICATIONS AND USAGE

Temporarily relieves muscle soreness and minor joint pains
in the wrist, knees, back,neck, hips, shoulders,elbows.

WARNINGS

For external use only

DO NOT USE

on wounds or damaged skin
with a heating pad or device
with other ointments, creams, sprays, or liniments
if you are allergic to any ingredients of this product.

WHEN USING

use only as directed
avoid contact with the eyes, mucous membranes, or rashes
do not bandage tightly

STOP USE

skin reactions such as redness, swelling, blistering or other discomfort occur
symptoms persist for more than 7 days

KEEP OUT OF REACH OF CHILDREN

lf swallowed accidentally, get medical help or contact
with Poison Control Center immediately

DOSAGE AND ADMINISTRATION

Adults and Children above 12 years old:
Clean and dry the affected area.
Tear off the protective film and apply the exposed part ofthe patch to the the affected area.
Carefully remove remaining film while pressing the patchfirmly on the skin.
Remove patch from the skin after at most 8-hourapplication.
Children under age of 12: Consult a doctor

INACTIVE INGREDIENT

Dihydroxyaluminum Aminoacetate
Edetate Disodium
Glycerin
Hydroxyacetophenone
Kaolin
Mineral Oil
Polyacrylic Acid
Polysorbate 80
PolyvinylPyrrolidone
Propylene Glycol
Sodium Polyacrylate
Tartaric Acid
Titanium Dioxide
Water